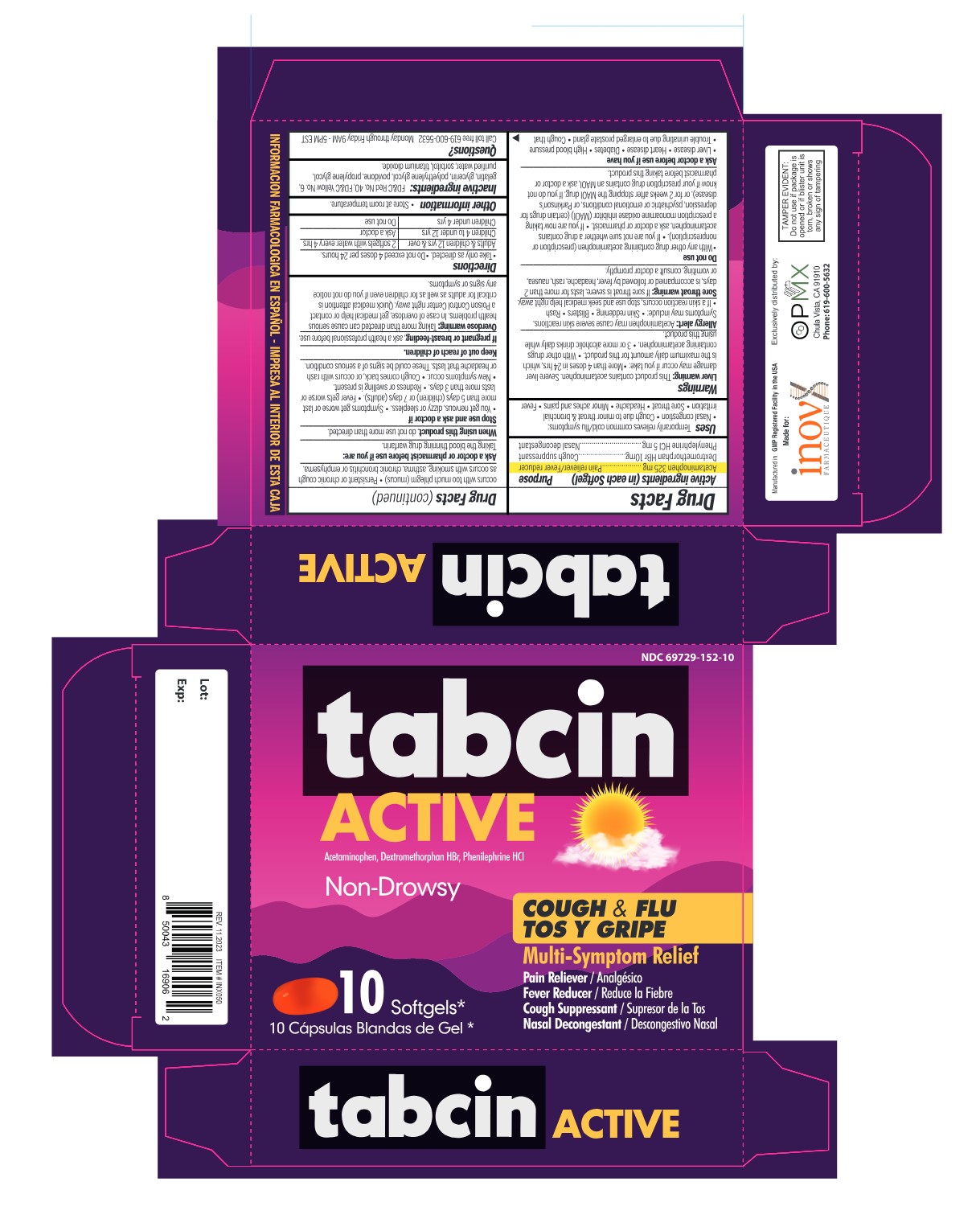 DRUG LABEL: tabcin ACTIVE
NDC: 69729-152 | Form: CAPSULE, LIQUID FILLED
Manufacturer: OPMX LLC.
Category: otc | Type: HUMAN OTC DRUG LABEL
Date: 20250829

ACTIVE INGREDIENTS: DEXTROMETHORPHAN HYDROBROMIDE 10 mg/1 1; ACETAMINOPHEN 325 mg/1 1; PHENYLEPHRINE HYDROCHLORIDE 5 mg/1 1
INACTIVE INGREDIENTS: FD&C YELLOW NO. 6; FD&C RED NO. 40; GELATIN; GLYCERIN; POLYETHYLENE GLYCOL, UNSPECIFIED; POVIDONE; PROPYLENE GLYCOL; WATER; SORBITOL; TITANIUM DIOXIDE

Tabcin Active

Drug Facts

ACTIVE INGREDIENT

Active ingredients (in each Softgel) | Purpose
Acetaminophen 325 mg | Pain reliever/Fever reducer
Dextromethorphan HBr 10 mg | Cough suppressant
Phenylephrine HCl 5 mg | Nasal decongestant

Uses

Temporarily relieves common cold/flu symptoms:

- Nasal congestion
- Cough due to minor throat & bronchial irritation
- Sore throat
- Headache
- Minor aches & pains
- Fever

Warnings

Liver warning

This product contains acetaminophen. Severe liver damage may occur if you take

- more than 4 doses in 24 hrs, which is the maximum daily amount for this product
- with other drugs containing acetaminophen
- 3 or more alcoholic drinks daily while using this product

Allergy alert

Acetaminophen may cause severe skin reactions. Symtoms may include.

Skin reddening blisters • rash • If a skin reaction occurs, stop use and seek medical help right away.

Sore throat warning

If sore throat is severe, lasts for more than 2 days, is accompanied or followed by fever, headache, rash, nausea, or vomiting, consult a doctor promptly.

Do not use

- with any other drug containing acetaminophen (prescription or nonprescription).
- If you are not sure whether a drug contains acetaminophen, ask a doctor or pharmacist.
- if you are now taking a prescription monoamine oxidase inhibitor (MAOI) (certain drugs for depression, psychiatric or emotional conditions, or Parkinson's disease), or for 2 weeks after stopping the MAOI drug.
- If you do not know if your prescription drug contains an MAOI, ask a doctor or pharmacist before taking this product.

Ask a doctor before use if you have

- Liver disease
- Heart disease
- Diabetes
- High blood pressure
- Trouble urinating due to enlarged prostate gland
- Cough that occurs with too much phlegm (mucus)
- Persistent or chronic cough as occurs with smoking, asthma, chronic bronchitis or emphysema.

Ask a doctor or pharmacist before use if you are

taking the blood thinning drug warfarin.

When using this product,

do not use more than directed.

Stop use and ask a doctor if

- You get nervouz, dizzy or sleepless.
- Symptoms get worse or last more than 5 days (children) or 7 days (adults).
- Fever gets worse or lasts more than 3 days.
- Redness or swelling is present.
- New symtoms occur.
- Cough comes back, or occurs with rash or headache that lasts. These could be signs of a serious condition.

Keep out of reach of children.

If pregnant or breast-feeding,

ask a health professional before use.

Overdose warning

Taking more than directed can cause serious health problems. In case of overdose, get medical help or contact a Poison Control Center right away. Quick medical attention is critical for adults as well for children even if you do not notice any signs or symptoms.

Directions

- Take only as directed.
- Do not exceed 4 doses per 24 hrs.

Adults & children 12 yrs & over | 2 softgels with water every 4 hrs
Children 4 to under 12 yrs | Ask a doctor
Children under 4 yrs | Do not use

Other information

Store at room temperature

Inactive ingredients

FD&C Red No. 40, FD&C Yellow No. 6, gelatin, glycerin, polyethylene glycol, povidone, propylene glycol, purified water, sorbitol special, titanium dioxide.

Questions?

Call to free 619-600-5632 Monday through Friday 9AM - 5PM EST

PRINCIPAL DISPLAY PANEL

NDC 69729-152-10

tabcin Active

Non-Drowsy

COUGH & FLU / TOS Y GRIPE

Multi-Symptom Relief

Acetaminophen, Dextromethorphan HBr, Phenylephrine HCl

- Pain Reliever/ Analgésico
- Fever Reducer/ Reduce la Fiebre
- Cough Suppressant / Supresor de la Tos
- Nasal Descongestant / Descongestivo Nasal

10 Softgels / 10 Cápsulas blandas de gel